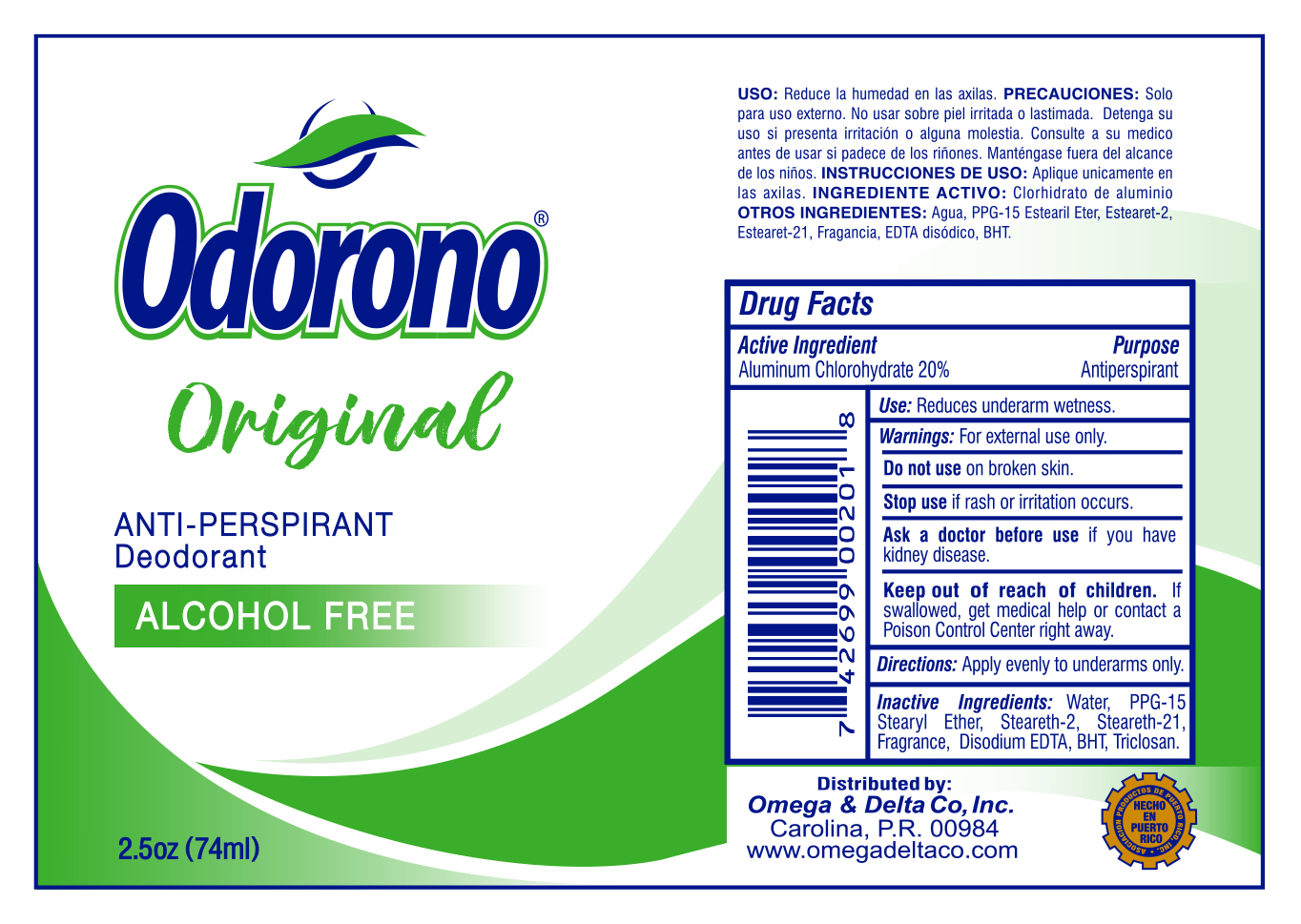 DRUG LABEL: Odorono
NDC: 51048-201 | Form: LIQUID
Manufacturer: Omega & Delta Co
Category: otc | Type: HUMAN OTC DRUG LABEL
Date: 20260121

ACTIVE INGREDIENTS: ALUMINUM CHLOROHYDRATE 20 g/100 mL
INACTIVE INGREDIENTS: WATER; PPG-15 STEARYL ETHER; STEARETH-2; STEARETH-21; EDETATE DISODIUM; BUTYLATED HYDROXYTOLUENE; TRICLOSAN

Odorono Antiperspirant Deodorant Roll-on Original

Drug Facts

Active Ingredients

Aluminum Chlorohydrate 20%

Purpose

Antiperspirant

INDICATIONS AND USAGE

Use: Reduces underarm wetness

Warnings: For external use only

Do not use on broken skin

Stop use if rash or irritation occurs

Ask a doctor before use if you have kidney disease

Keep out of reach of children. If swallowed, get medical help or contact a Poison Control Center.

DOSAGE AND ADMINISTRATION

Directions: Apply evenly to underarms only

INACTIVE INGREDIENT

Inactive Ingredients: Water, PPG-15 Stearyl Ether, Steareth-2, Steareth-21, Fragrance, Disodium EDTA, BHT, Triclosan

Hecho en Puerto Rico por:

Omega & Delta Co., Inc.

P.O. Box 1831, Carolina, P.R. 00984